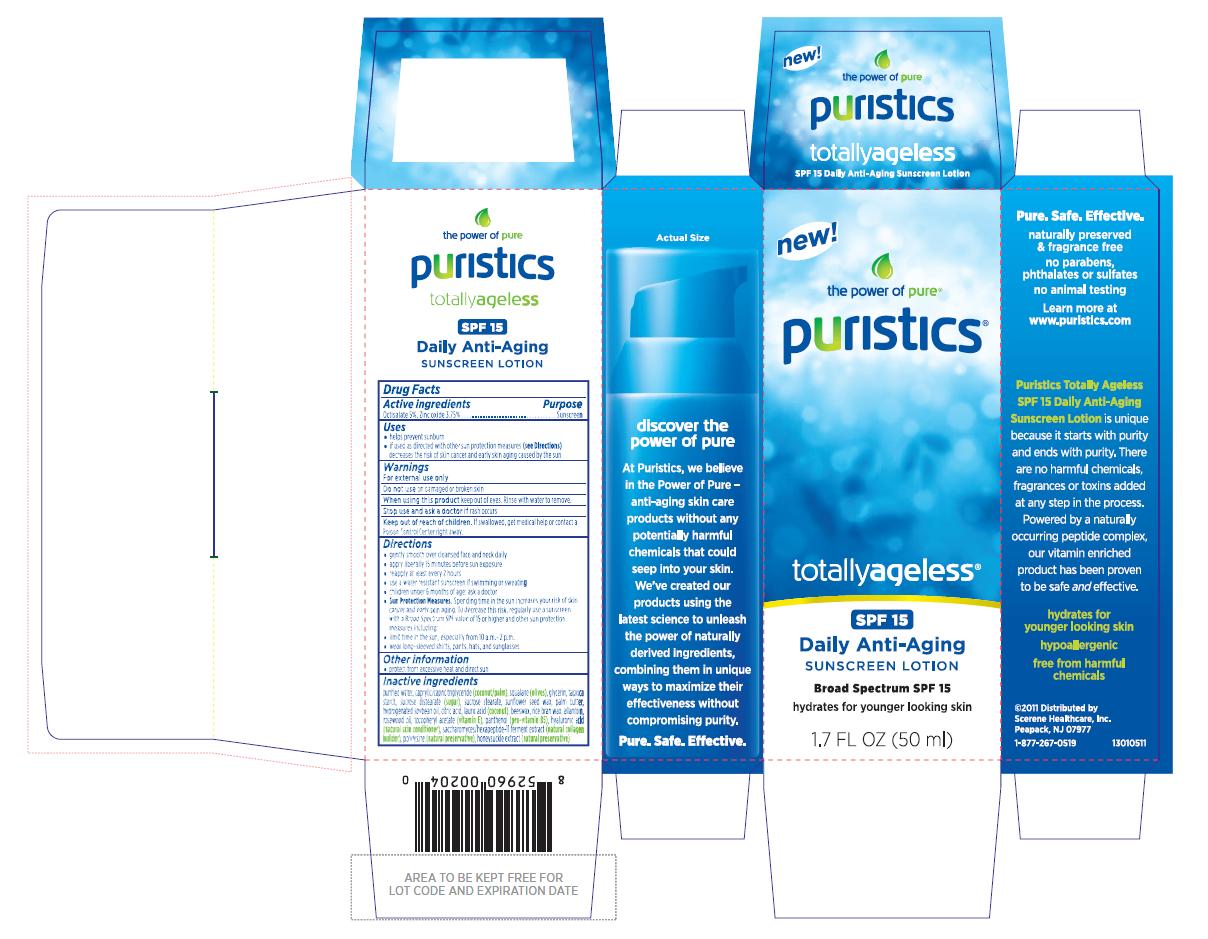 DRUG LABEL: puristics totallyageless spf 15 daily anti-aging 
NDC: 76026-304 | Form: LOTION
Manufacturer: Scerene Healthcare, Inc.
Category: otc | Type: HUMAN OTC DRUG LABEL
Date: 20111201

ACTIVE INGREDIENTS: Octisalate 5 mL/100 mL; Zinc Oxide 3.75 mL/100 mL
INACTIVE INGREDIENTS: Water; Medium-chain Triglycerides; Squalane; Glycerin; Starch, Tapioca; Sucrose Distearate; Sucrose Stearate; Helianthus Annuus Seed Wax; Elaeis Guineensis Fruit Butter; Hydrogenated Soybean Oil; Citric Acid Monohydrate; Lauric Acid; Yellow Wax; Rice Bran; Allantoin; Rosewood Oil; .alpha.-tocopherol Acetate; Panthenol; Hyaluronic Acid; Lonicera Caprifolium Flower; Lonicera Japonica Flower

puristic® totallyageless® SPF 15 Daily Anti-Aging Sunscreen Lotion
Drug Facts

Active ingredients

Octisalate 5%
Zinc oxide 3.75%

Purpose

Sunscreen

Uses

- helps prevent sunburn
- if used as directed with other sun protection measures (see Directions) decreases the risk of skin cancer and early skin aging caused by the sun

Warnings

For external use only
Do not use on damaged or broken skin
When using the product keep out of eyes. Rinse with water to remove.
Stop use and ask a doctor if rash occurs

Keep out of reach of children.

If swallowed, get medical help or contact a PoisonControlCenter right away.

Directions

- gently smooth over cleansed face and neck daily
- apply liberally 15 minutes before sun exposure
- reapply at least every 2 hours
- use a water resistant sunscreen if swimming or sweating
- children under 6 months of age: ask a doctor
- Sun Protection Measures. Spending time in the sun increases your risk of skin cancer and early skin aging. To decrease this risk, regularly use a sunscreen with a Broad Spectrum SPF value of 15 or higher and other sun protection measures including:
- limit time in the sun, especially from 10 a.m.-2 p.m.
- wear long-sleeved shirts, pants, hats, and sunglasses

Other information

- protect from excessive heat and direct sun

Inactive ingredients

purified water, caprylic/capric triglyceride (coconut/palm), squalane (olives), glycerin, tapioca starch, sucrose distearate (sugar), sucrose stearate, sunflower seed wax, palm butter, hydrogenated soybean oil, citric acid, lauric acid (coconut), beeswax, rice bran wax, allantoin, rosewood oil, tocopheryl acetate (vitamin E), panthenol (pro-vitamin B5), hyaluronic acid (natural skin conditioner), saccharomyces/hexapeptide-11 ferment extract (natural collagen builder), polylysine (natural preservative), honeysuckle extract (natural preservative)

Principal panel display

new!

the power of pure®

puristics®

totallyageless®

SPF 15

Daily Anti-Aging

SUNSCREEN LOTION

Broad Spectrum SPF 15

hydrates for younger looking skin

1.7 FL OZ (50 ml)

Pure. Safe. Effective.
naturally preserved & fragrance free
no parabens, phthalates or sulfates
no animal testing
Learn more at www.puristics.com

Puristics Totally Ageless SPF 15 Daily Anti-Aging Sunscreen Lotion is unique because it starts with purity and ends with purity. There are no harmful chemicals, fragrances or toxins added at any step in the process. Powered by a naturally occurring peptide complex, our vitamin enriched product has been proven to be safe and effective.

hydrates for younger looking skin

hypoallergenic

free from harmful chemicals

©2011 Distributed by
Scerene Healthcare, Inc.
Peapack, NJ 07977
1-877-267-0519
13010511

Actual Size

discover the power of pure

At Puristics, we believe in the Power of Pure - anti-aging skin care products without any potentially harmful chemicals that could seep into your skin. We’ve created our products using the latest science to unleash the power of naturally derived ingredients, combining them in unique ways to maximize their effectiveness without compromising purity.

Pure. Safe. Effective.